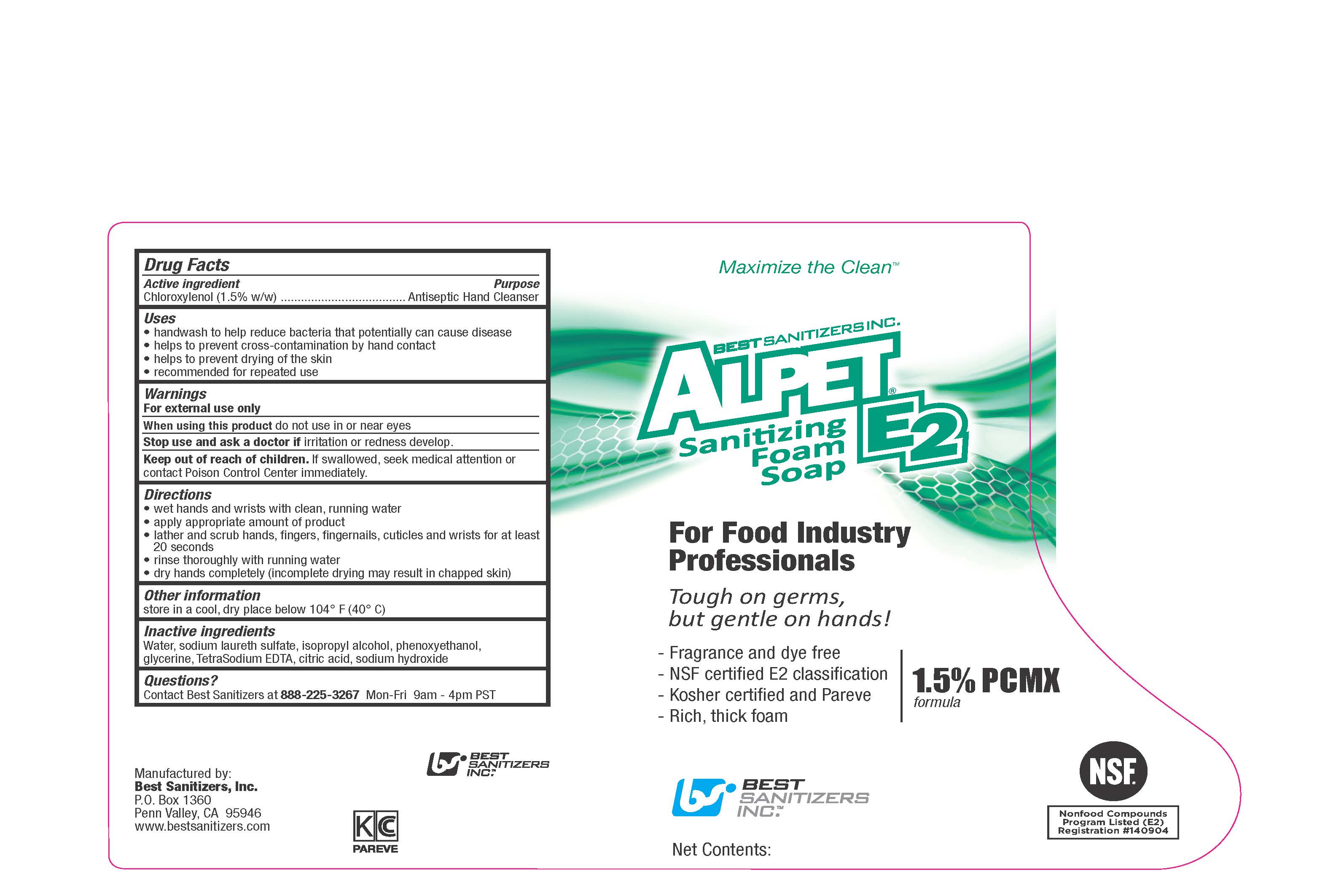 DRUG LABEL: ALPET E2 Sanitizing Foam
NDC: 59900-128 | Form: LIQUID
Manufacturer: Best Sanitizers, Inc.
Category: otc | Type: HUMAN OTC DRUG LABEL
Date: 20241205

ACTIVE INGREDIENTS: CHLOROXYLENOL 15 mg/1 mL
INACTIVE INGREDIENTS: WATER; SODIUM LAURETH-3 SULFATE; ISOPROPYL ALCOHOL; PHENOXYETHANOL; GLYCERIN; EDETATE SODIUM; CITRIC ACID MONOHYDRATE; SODIUM HYDROXIDE

Drug Facts 5900-128

Active ingredient

Chloroxylenol (1.5% w/w)

Purpose

Antiseptic Hand Cleanser

Uses

- handwash to help reduce bacteria that potentially can cause disease

- helps prevent cross-contamination by hand contact

- helps to prevent drying of the skin

- recommended for repeated use

Warnings

For external use only

WHEN USING

When using this productdo not use in or near eyes

Stop use and ask a doctor ifirritation or redness develop.

Keep out of reach of children.

If swallowed, seek medical attention or contact Poison Control Center immediately.

Directions

- wet hands and wrists with clean, running water

- apply appropriate amount of product

- lather and scrub hands, fingers, fingernails, cuticles and wrists for at least 20 seconds

- rinse thoroughly with running water

- dry hands completely (incomplete drying may result in chapping skin)

Other information

store in a cool, dry place below 104oF (40oC)

Inactive ingredients

Water, sodium laureth sulfate, isopropyl alcohol, phenoxyethanol, glycerine, TetraSodium EDTA, citric acid, sodium hydroxide

Questions?

Contact Best Sanitizers at 888-225-3267Mon-Fri 9am-4 pm PST

PACKAGE LABEL

Maximize the Clean

BEST SANITIZERS INC.

ALPET E2

Sanitizing

Foam

Soap

For Food Industry

Professionals

Tough on germs,

but gentle on hands!

Fragrance and dye free

NSF certified E2 classification

Kosher certified and Pareve

Rich, thick foam

1.5% PCMX

formula

BEST

SANITIZERS

INC.

NSF

Nonfood Compounds

Program Listed (E2)

Registration Number 140904

Net Contents: